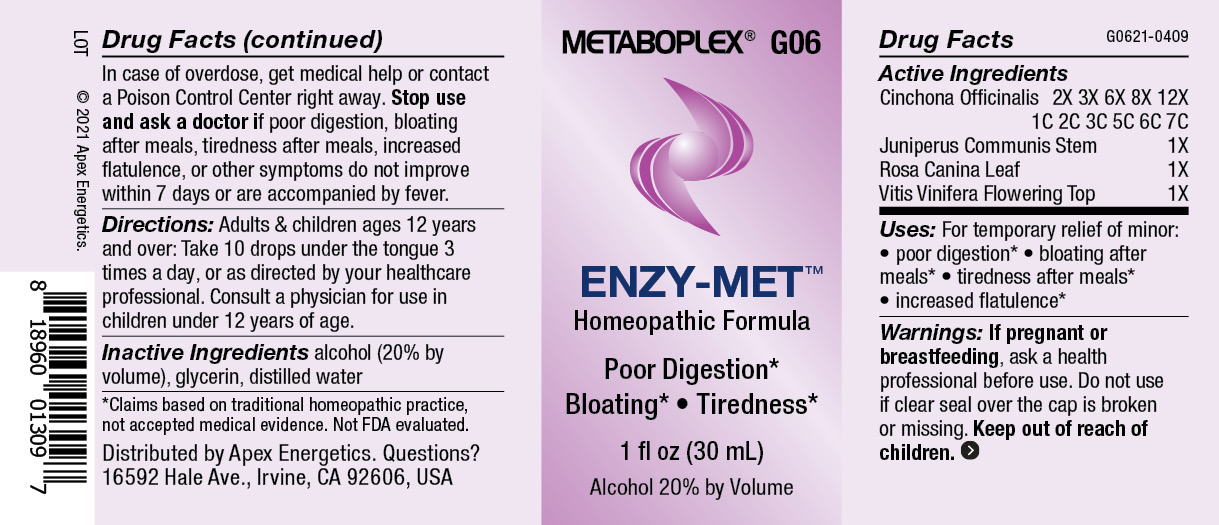 DRUG LABEL: G06
NDC: 63479-0706 | Form: SOLUTION/ DROPS
Manufacturer: Apex Energetics Inc.
Category: homeopathic | Type: HUMAN OTC DRUG LABEL
Date: 20240108

ACTIVE INGREDIENTS: ROSA CANINA LEAF 1 [hp_X]/1 mL; VITIS VINIFERA FLOWERING TOP 1 [hp_X]/1 mL; CINCHONA OFFICINALIS BARK 7 [hp_C]/1 mL; JUNIPERUS COMMUNIS STEM 1 [hp_X]/1 mL
INACTIVE INGREDIENTS: WATER; ALCOHOL; GLYCERIN

G06

Active Ingredients
Cinchona Officinalis | 2X 3X 6X 8X 12X 1C 2C 3C 5C 6C 7C
Juniperus Communis Stem | 1X
Rosa Canina Leaf | 1X
Vitis Vinifera Flowering Top | 1X

INDICATIONS AND USAGE

Uses:

For temporary relief of minor:

poor digestion*

bloating after meals*

tiredness after meals*

increased flatulence*

*Claims based on traditional homeopathic practice, not accepted medical evidence. Not FDA evaluated.

WARNINGS

PREGNANCY OR BREAST FEEDING

If pregnant or breastfeeding, ask a health professional before use.

Do not use if clear seal over the cap is broken or missing.

Keep out of reach of children. In case of overdose, get medical help or contact a Poison Control Center right away.

Stop use and ask a doctor if poor digestion, bloating after meals, tiredness after meals, increased flatulence, or other symptoms do not improve within 7 days or are accompanied by fever.

Directions:

Adults & children ages 12 years and over: Take 10 drops under the tongue 3 times a day, or as directed by your healthcare professional. Consult a physician for use in children under 12 years of age.

Inactive Ingredients

alcohol (20% by volume), glycerin, distilled water

Distributed by Apex Energetics. Questions?

16592 Hale Ave., Irvine, CA 92606, USA

PACKAGE LABEL

METABOPLEX® G06

ENZY-MET™

Homeopathic Formula

Poor Digestion*

Bloating* Tiredness*

1 fl oz (30 mL)

Alcohol 20% by Volume